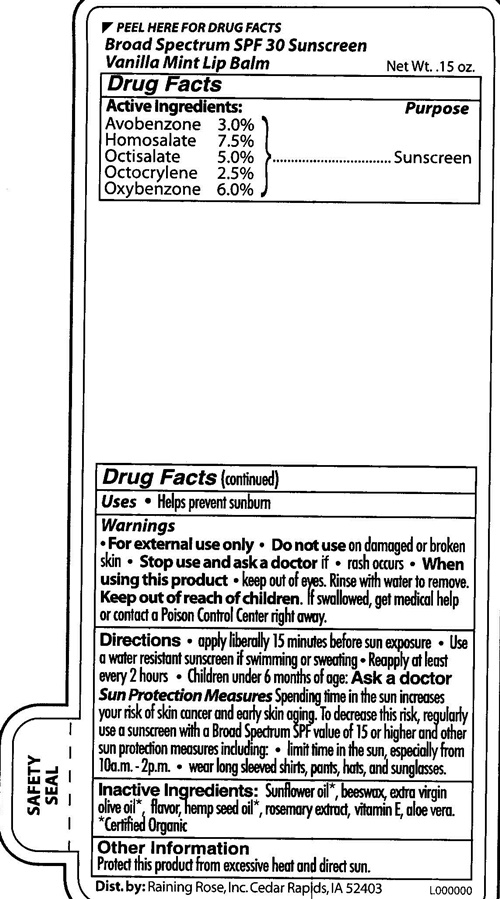 DRUG LABEL: Vanilla Mint Lip
NDC: 65692-0201 | Form: STICK
Manufacturer: Raining Rose, Inc.
Category: otc | Type: HUMAN OTC DRUG LABEL
Date: 20170123

ACTIVE INGREDIENTS: AVOBENZONE 0.12 g/4.25 g; HOMOSALATE 0.32 g/4.25 g; OCTISALATE 0.21 g/4.25 g; OCTOCRYLENE 0.10 g/4.25 g; OXYBENZONE 0.25 g/4.25 g
INACTIVE INGREDIENTS: SUNFLOWER OIL; YELLOW WAX; OLIVE OIL; CANNABIS SATIVA SEED OIL; ROSEMARY; .ALPHA.-TOCOPHEROL; ALOE VERA LEAF

RR Vanilla Mint Lip Balm - 0201

PEEL HERE FOR DRUG FACTS BROAD SPECTRUN SPF 30 Sunscreen Vanilla Mint Lip Balm - 0201

Active Ingredients:

Avobenzone 3.0%
Homosalate 7.5%
Octisalate 5.0%
Octocrylene 2.5%
Oxybenzone 6.0%

Purpose

Sunscreen

Uses

- Helps prevent sunburn

Warnings

For External Use Only

Do not use

on damaged or broken skin

Stop use and as a doctor if

- rash occurs

When using this product

- Keep out of eyes.

Rinse well with water to remove.

Keep out of reach of children.

If swalowed, get medical help or call a Poison Control Center right away.

Directions

- apply liberally 15 minutes before sun exposure
- use a water resistant sunscreen if swimming or sweating
- Reapply at least every 2 hours
- Children under 6 months of age: Ask a doctor

Sun Protection Measures

Spending time in the sun increases your risk of skin cancer and early skin aging. To decrease this risk, regularly use a sunscreen with a Broad Spectrum SPF value of 15 or higher and other protection measures including:

- limit time in the sun, s\especially from 10a.m. - 2p.m.
- wear long slessved shirts, pants, hat, and sunglasses.

Inactive Ingredients:

Sunflower oil*, beeswax, extra virgin olive oil*, flavor hemp seed oil*, rosemary extract, vitamin E, Aloe vera.

*Certified Organic

Other Information

Protect this product from excessive heart and direct sun.

Vanilla Mint Lip Balm SPF 30 product label

Dist. by: Raining Rose, Inc. Cedar Rapids, IA 52403